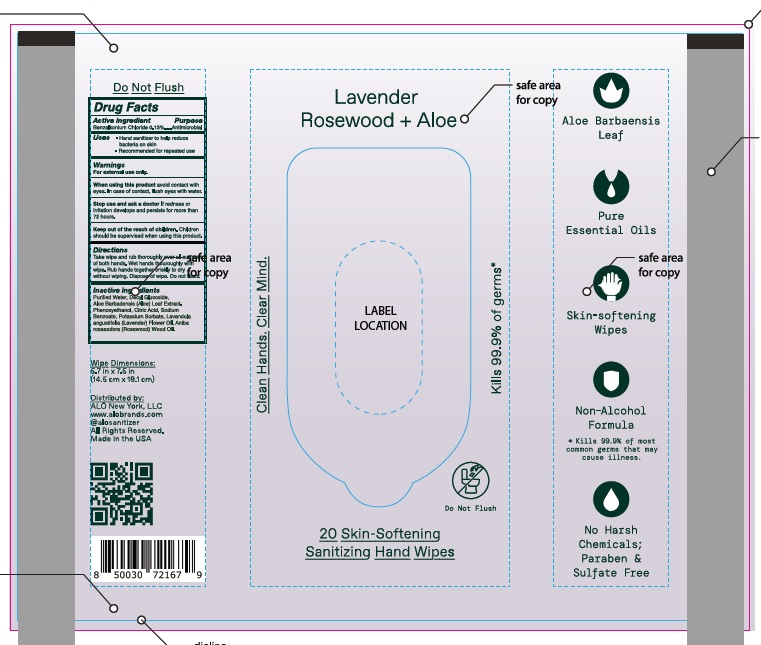 DRUG LABEL: Benzalkonium Chloride
NDC: 82355-552 | Form: CLOTH
Manufacturer: ALO NEW YORK LLC
Category: otc | Type: HUMAN OTC DRUG LABEL
Date: 20260115

ACTIVE INGREDIENTS: BENZALKONIUM CHLORIDE 0.0013 mg/100 mg
INACTIVE INGREDIENTS: ALOE VERA LEAF; PHENOXYETHANOL; SODIUM BENZOATE; DECYL GLUCOSIDE; CITRIC ACID MONOHYDRATE; POTASSIUM SORBATE; LAVANDULA ANGUSTIFOLIA FLOWER; ANIBA ROSAEODORA WHOLE; WATER

Peppermint Eucalyptus + Aloe

Active ingredients

Benzalkonium Chloride 0.13%

Purpose

Antimicrobial

Uses

- Hand Sanitizer to help reduce bacteria on the skin
- Recommended for repeated use

Warnings

For external use only.

When using this product

avoid contact with eyes. In case of contact, flush with water.

Stop use and ask a doctor

If redness or irritation develops and persists for more than 72 hours

Keep out of reach of children

Children should be supervised when using this product

Directions

Take wipe and rub thoroughly over all surface of both hands. Wet hands thoroughly with wipes. Rub hand together briskly to dry without wiping. Dispose of wipe. Do not flush.

Inactive ingredients

Purified Water, Decyl Glucoside, Aloe Barbadensis (Aloe) Leaf Extract, Phenoxyethanol, Citric Acid, Sodium Benzoate, Potassium Sorbate, Eucalyptus Globulus Oil, Mentha Piperita (Peppermint) Oil.

Principal Display Panel

Lavender Rosewood + Aloe

ALOH

Clean Hands, Clear Mind

Kills 99.9% of Germs*

20 Skin-Softening Sanitizing Hand Wipes

Do Not Peel